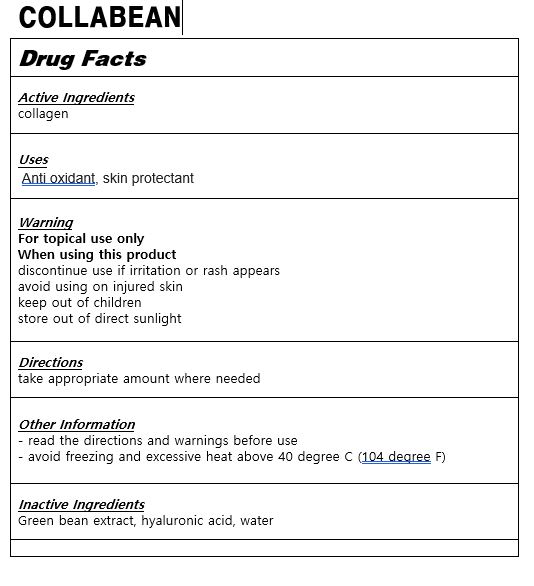 DRUG LABEL: COLLABEAN
NDC: 83113-0003 | Form: LIQUID
Manufacturer: eveskorea
Category: otc | Type: HUMAN OTC DRUG LABEL
Date: 20221121

ACTIVE INGREDIENTS: HYDROLYSED MARINE COLLAGEN (ENZYMATIC; 2000 MW) 5 g/100 mL
INACTIVE INGREDIENTS: STRING BEAN; HYALURONIC ACID

Drug Facts

ACTIVE INGREDIENT

COLLAGEN

PURPOSE

Anti oxidant, skin protectant

KEEP OUT OF REACH OF THE CHILDREN

INDICATIONS AND USAGE

take proper amount where needed

Keep out of reach of children.

Irritation around the eyes, ears, mucous membranes, including the mouth, under the skin irritation and rashes

Store in the room temperature

DOSAGE AND ADMINISTRATION

for oral use only

INACTIVE INGREDIENT

sucralfate, glutathione,